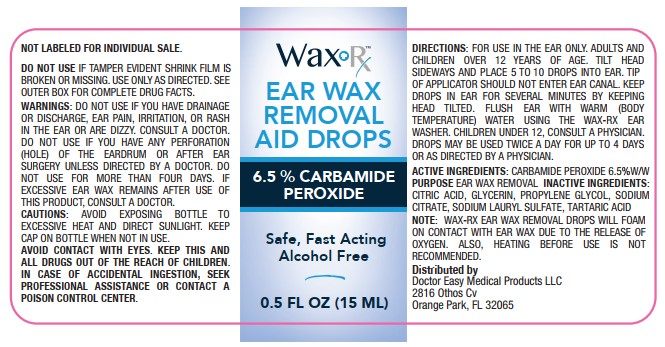 DRUG LABEL: WaxRx Ear Wax Removal Aid Drops
NDC: 72724-001 | Form: LIQUID
Manufacturer: DOCTOR EASY MEDICAL PRODUCTS, LLC
Category: otc | Type: HUMAN OTC DRUG LABEL
Date: 20250501

ACTIVE INGREDIENTS: CARBAMIDE PEROXIDE 6.5 g/100 mL
INACTIVE INGREDIENTS: TARTARIC ACID; GLYCERIN; CITRIC ACID MONOHYDRATE; SODIUM CITRATE; SODIUM LAURYL SULFATE; PROPYLENE GLYCOL

ACTIVE INGREDIENT

Carbamide Peroxide 6.5%

PURPOSE

Carbamide Peroxide 6.5%...................Earwax Removal Aid

INDICATIONS AND USAGE

For occasional use as an aid to soften, loosen and remove excessive ear wax

Ask a doctor before use if you have
• ear drainage or discharge

• ear pain

• irritation or rash in the ear
• dizziness

• an injury or perforation (hole) of the ear drum
• recently had ear surgery

Stop use and ask a doctor if
• you need to use for more than 4 days
• excessive ear wax remains after use of this product

When using this productdo not get into eyes

Keep out of reach of children.In case of accidental overdose or allergic
reaction, get medical help or contact a Posion Control Center immediately

FOR USE IN THE EAR ONLY

Adults and children over 12 years of age.Tilt head sideways and place 5-10 drops into ear. Tip of applicator should not enter ear canal. Keep drops in ear for several minutes by keeping head tilted or placing cotton in ears. Flush ear with VERY WARM (body temperature) water using the Wax-Rx Ear Washer.

Children under 12, consult a physician. Drops my be used twice daily for up to 4 days or as directed by a physician.

STORAGE AND HANDLING

• Avoid exposing bottle to excessive heat or direct sunlight.
• Product foams on contact with ear wax due to release of oxygen. There may be an associated crackling

• Keep cap on bottle when not in use.
• Lot no. and exp. date:see Label, bottom contained or box.

INACTIVE INGREDIENT

Citric Acid, Glycerin, Propylene Glycol, Sodium Citrate, Sodium Lauryl Sulfate, Tartaric Acid

PACKAGE LABEL

WaxRx

EAR WAX

REMOVAL

AID DROPS

6.5% Carbamide Peroxide

Safe, Fast Acting

Alcohol Free

0.5 FL OZ (15 ML)